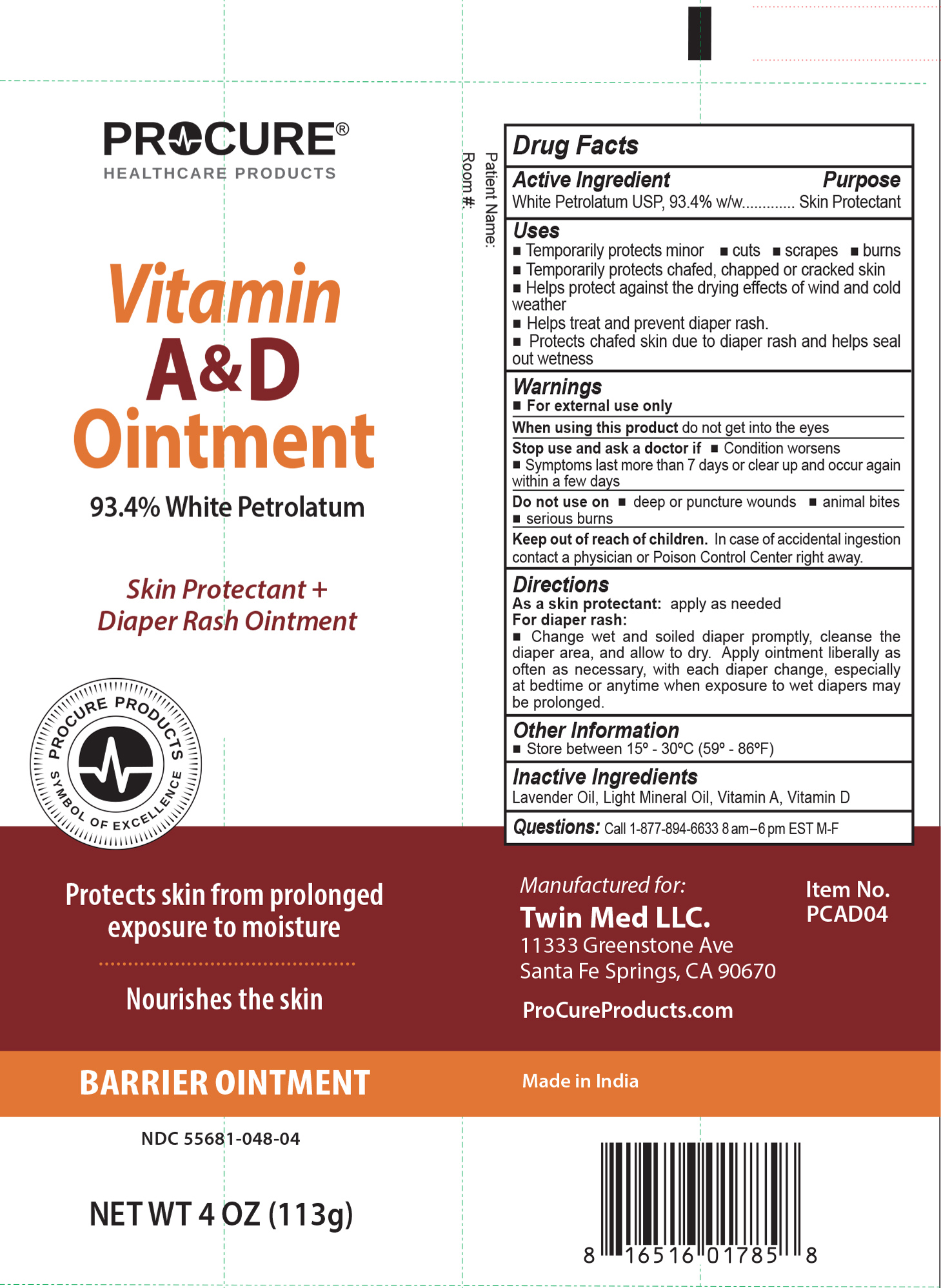 DRUG LABEL: ProCure Vitamin A and D
NDC: 55681-048 | Form: OINTMENT
Manufacturer: Twin Med LLC
Category: otc | Type: HUMAN OTC DRUG LABEL
Date: 20251201

ACTIVE INGREDIENTS: WHITE PETROLATUM 93.4 g/100 g
INACTIVE INGREDIENTS: VITAMIN D; VITAMIN A PALMITATE; LIGHT MINERAL OIL; LAVENDER OIL

Active Ingredient

White Petrolatum USP, 93.4% w/w

Purpose

Skin Protectant

Uses

- Temporarily protects minor: cuts, scrapes and burns
- Temporarily protects chafed, chapped or cracked skin
- Helps protect against the drying effects of wind and cold weather
- Helps treat and prevent diaper rash. Protects chafed skin due to diaper rash and helps seal out wetness

Warnings

For external use only

When using this product do not get into the eyes

Stop use and ask a doctor if

- Condition worsens
- Symptoms last more than 7 days or clear up and occur again within a few days

Do not use on

- deep or puncture wounds
- animal bites
- serious burns

Keep out of reach of children. In case of accidental ingestion contact a physician or Poison Control Center right away.

Directions

- As a skin protectant: apply as needed
- For diaper rash: Change wet and soiled diaper promptly, cleanse the diaper area, and allow to dry. Apply ointment liberally as often as necessary, with each diaper change, especially at bedtime or anytime when exposure to wet diapers may be prolonged.

Inactive Ingredients

Inactive Ingredients: Lavender Oil, Light Mineral Oil, Vitamin A, Vitamin D